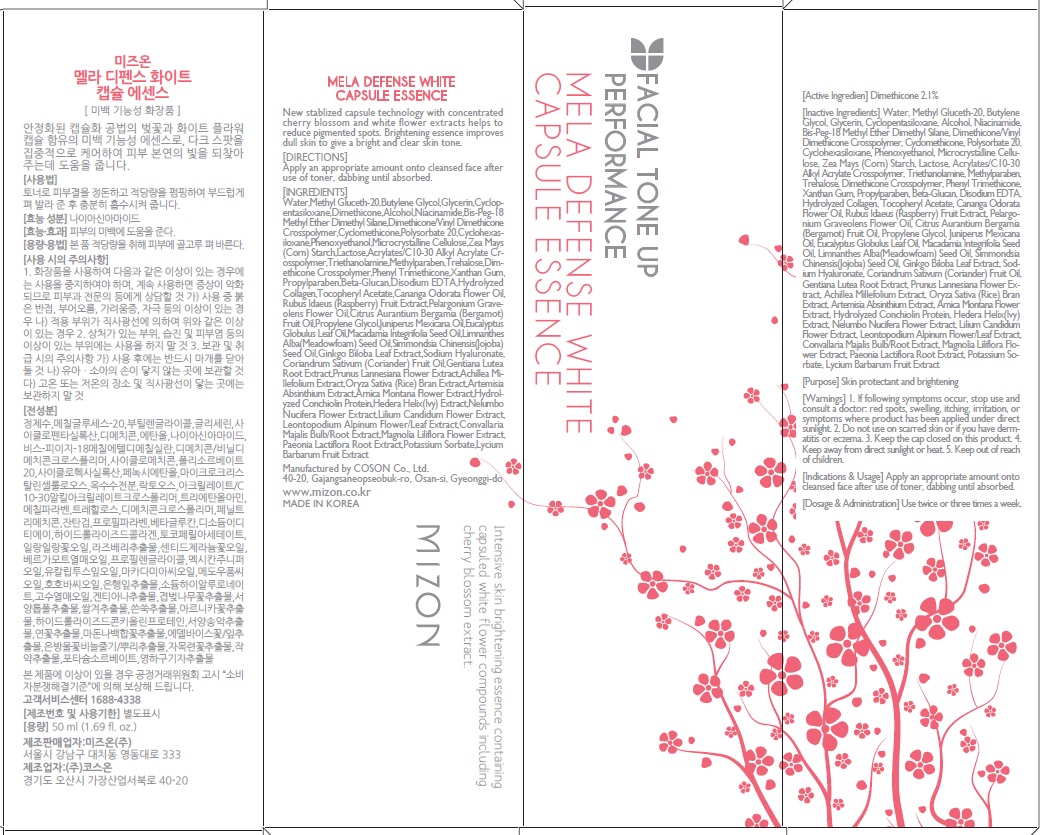 DRUG LABEL: MELA DEFENSE WHITE ESSENCE
NDC: 57718-120 | Form: GEL
Manufacturer: MIZON CO., LTD.
Category: otc | Type: HUMAN OTC DRUG LABEL
Date: 20160407

ACTIVE INGREDIENTS: Dimethicone 1.05 g/50 mL
INACTIVE INGREDIENTS: Water; Methyl Gluceth-20

ACTIVE INGREDIENT

Active Ingredient: Dimethicone 2.1%

INACTIVE INGREDIENT

Inactive Ingredients: Water, Methyl Gluceth-20, Butylene Glycol, Glycerin, Cyclopentasiloxane, Alcohol, Niacinamide, Bis-Peg-18 Methyl Ether Dimethyl Silane, Dimethicone/Vinyl Dimethicone Crosspolymer, Cyclomethicone, Polysorbate 20, Cyclohexasiloxane, Phenoxyethanol, Microcrystalline Cellulose, Zea Mays (Corn) Starch, Lactose, Acrylates/C10-30 Alkyl Acrylate Crosspolymer, Triethanolamine, Methylparaben, Trehalose, Dimethicone Crosspolymer, Phenyl Trimethicone, Xanthan Gum, Propylparaben, Beta-Glucan, Disodium EDTA, Hydrolyzed Collagen, Tocopheryl Acetate, Cananga Odorata Flower Oil, Rubus Idaeus (Raspberry) Fruit Extract, Pelargonium Graveolens Flower Oil, Citrus Aurantium Bergamia (Bergamot) Fruit Oil, Propylene Glycol, Juniperus Mexicana Oil, Eucalyptus Globulus Leaf Oil, Macadamia Integrifolia Seed Oil, Limnanthes Alba(Meadowfoam) Seed Oil, Simmondsia Chinensis(Jojoba) Seed Oil, Ginkgo Biloba Leaf Extract, Sodium Hyaluronate, Coriandrum Sativum (Coriander) Fruit Oil, Gentiana Lutea Root Extract, Prunus Lannesiana Flower Extract, Achillea Millefolium Extract, Oryza Sativa (Rice) Bran Extract, Artemisia Absinthium Extract, Arnica Montana Flower Extract, Hydrolyzed Conchiolin Protein, Hedera Helix(Ivy) Extract, Nelumbo Nucifera Flower Extract, Lilium Candidum Flower Extract, Leontopodium Alpinum Flower/Leaf Extract, Convallaria Majalis Bulb/Root Extract, Magnolia Liliflora Flower Extract, Paeonia Lactiflora Root Extract, Potassium Sorbate, Lycium Barbarum Fruit Extract

PURPOSE

Purpose: Skin protectant and brightening

WARNINGS

Warnings: 1. If following symptoms occur, stop use and consult a doctor: red spots, swelling, itching, irritation, or symptoms where product has been applied under direct sunlight. 2. Do not use on scarred skin or if you have dermatitis or eczema. 3. Keep the cap closed on this product. 4. Keep away from direct sunlight or heat. 5. Keep out of reach of children.

KEEP OUT OF REACH OF CHILDREN

INDICATIONS & USAGE

Indications & Usage: Apply an appropriate amount onto cleansed face after use of toner, dabbing until absorbed.

DOSAGE & ADMINISTRATION

Dosage & Administration: Use twice or three times a week.